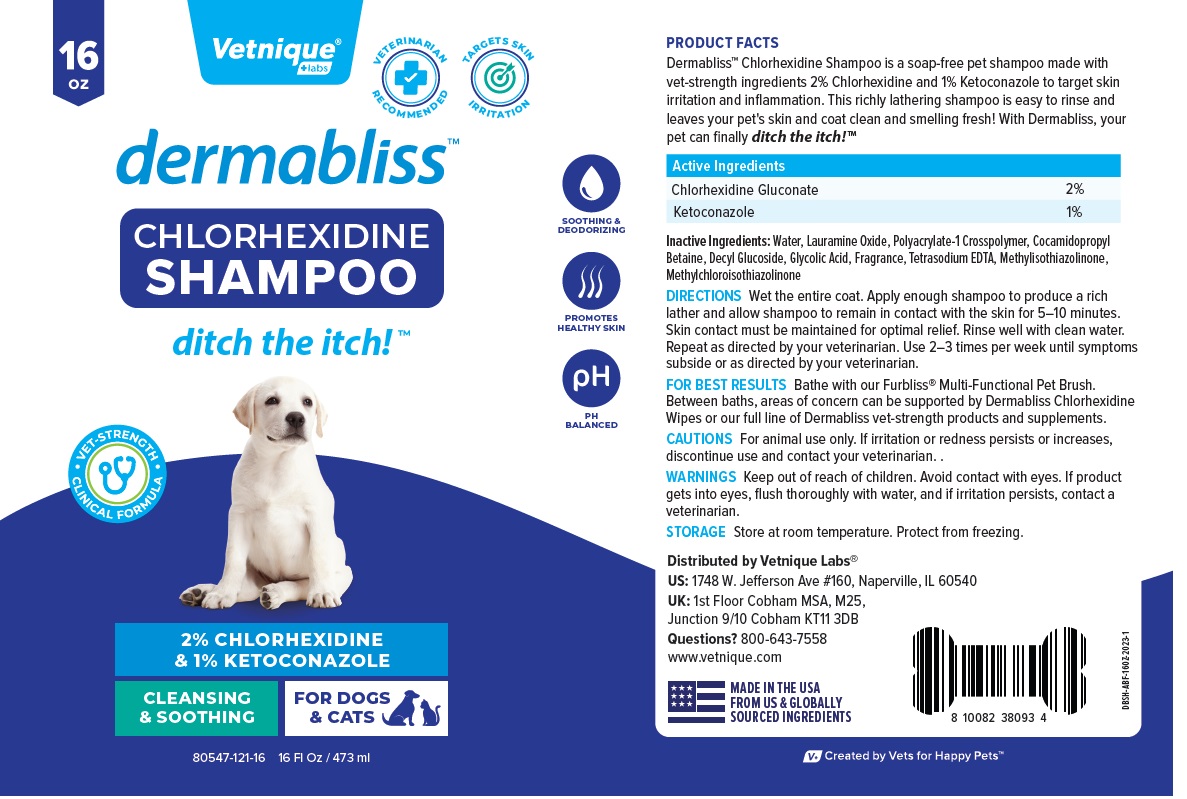 DRUG LABEL: dermabliss
NDC: 80547-121 | Form: SHAMPOO
Manufacturer: Vetnique Labs LLC
Category: animal | Type: OTC ANIMAL DRUG LABEL
Date: 20230811

ACTIVE INGREDIENTS: CHLORHEXIDINE GLUCONATE 20 mg/1 mL; KETOCONAZOLE 10 mg/1 mL
INACTIVE INGREDIENTS: WATER; LAURAMINE OXIDE; POLYACRYLATE-1 CROSSPOLYMER; COCAMIDOPROPYL BETAINE; DECYL GLUCOSIDE; GLYCOLIC ACID; EDETATE SODIUM; METHYLISOTHIAZOLINONE; METHYLCHLOROISOTHIAZOLINONE

dermabliss™ CHLORHEXIDINE SHAMPOO

Active Ingredients

Chlorhexidine Gluconate 2%
Ketoconazole 1%

INDICATIONS AND USAGE

PRODUCT FACTS
Dermabliss™ Chlorhexidine Shampoo is a soap-free pet shampoo made with vet-strength ingredients 2% Chlorhexidine and 1% Ketoconazole to target skin irritation and inflammation. This richly lathering shampoo is easy to rinse and leaves your pet's skin and coat clean and smelling fresh! With Dermabliss, your pet can finally ditch the itch!™

INACTIVE INGREDIENT

Inactive Ingredients: Water, Lauramine Oxide, Polyacrylate-1 Crosspolymer, Cocamidopropyl Betaine, Decyl Glucoside, Glycolic Acid, Fragrance, Tetrasodium EDTA, Methylisothiazolinone, Methylchloroisothiazolinone

DOSAGE AND ADMINISTRATION

DIRECTIONS Wet the entire coat. Apply enough shampoo to produce a rich lather and allow shampoo to remain in contact with the skin for 5–10 minutes. Skin contact must be maintained for optimal relief. Rinse well with clean water. Repeat as directed by your veterinarian. Use 2–3 times per week until symptoms subside or as directed by your veterinarian.

FOR BEST RESULTS Bathe with our Furbliss® Multi-Functional Pet Brush. Between baths, areas of concern can be supported by Dermabliss Chlorhexidine Wipes or our full line of Dermabliss vet-strength products and supplements.

PRECAUTIONS

CAUTIONS For animal use only. If irritation or redness persists or increases, discontinue use and contact your veterinarian.

WARNINGS

WARNINGS Keep out of reach of children. Avoid contact with eyes. If product gets into eyes, flush thoroughly with water, and if irritation persists, contact a veterinarian.

STORAGE Store at room temperature. Protect from freezing.

VETERINARIAN RECOMMENDED

TARGETS SKIN IRRITATION

SOOTHING & DEODORIZING

PROMOTES HEALTHY SKIN

PH BALANCED

• VET-STRENGTH • CLINICAL FORMULA

CLEANSING & SOOTHING

FOR DOGS & CATS

Distributed by Vetnique Labs®

US: 1748 W. Jefferson Ave #160, Naperville, IL 60540

UK: 1st Floor Cobham MSA, M25,
Junction 9/10 Cobham KT11 3DB

Questions? 800-643-7558

www.vetnique.com

MADE IN THE USA FROM US & GLOBALLY SOURCED INGREDIENTS

V+ Created by Vets for Happy Pets™